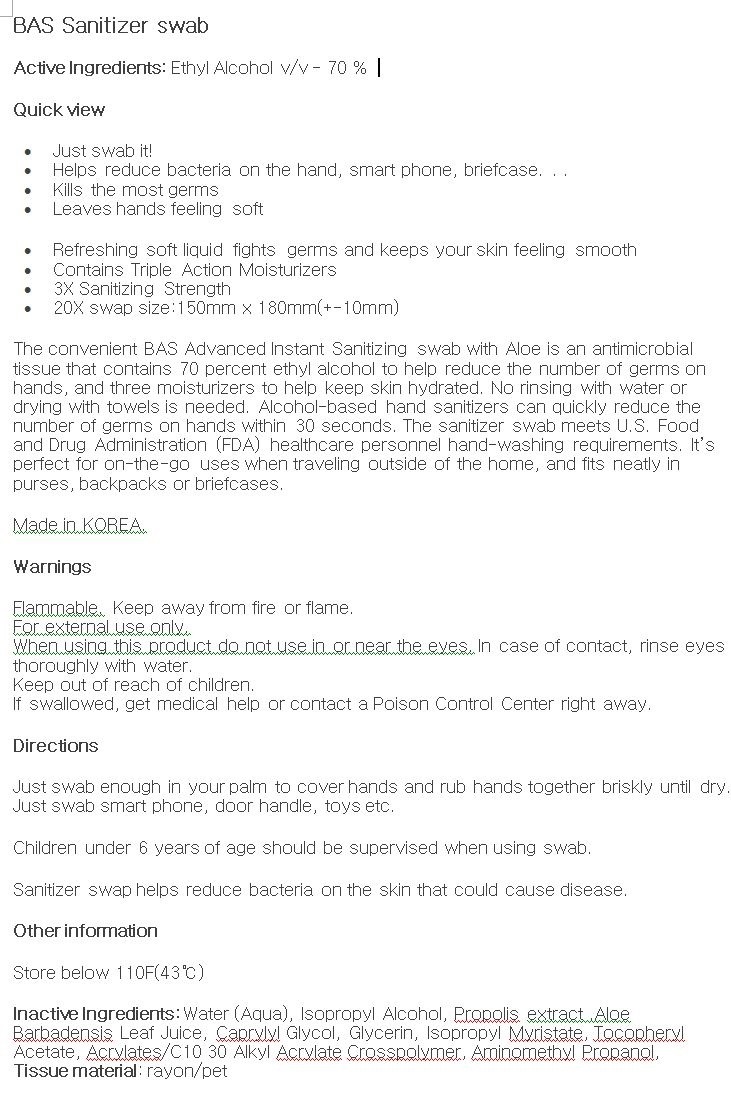 DRUG LABEL: BAS Sanitizer swab
NDC: 74085-0002 | Form: LIQUID
Manufacturer: BIOCHEM KOREA CO LTD
Category: otc | Type: HUMAN OTC DRUG LABEL
Date: 20201224

ACTIVE INGREDIENTS: ALCOHOL 70 g/100 g
INACTIVE INGREDIENTS: BIS-OLEAMIDO ISOPROPYL ALCOHOL; GLYCERIN; WATER; ISOPROPYL MYRISTATE

Drug Facts

ACTIVE INGREDIENT

ethyl alcohol

PURPOSE

The convenient Sense Fresh Advanced Instant Hand Sanitizer with Aloe is an antimicrobial liquid that contains 70 percent ethyl alcohol to help reduce the number of germs on hands, and three moisturizers to help keep skin hydrated. No rinsing with water or drying with towels is needed. Alcohol-based hand sanitizers can quickly reduce the number of germs on hands within 30 seconds. The hand sanitizer meets U.S. Food and Drug Administration (FDA) healthcare personnel hand-washing requirements. It’s perfect for on-the-go uses when traveling outside of the home, and fits neatly in purses, backpacks or briefcases.

KEEP OUT OF REACH OF THE CHILDREN

INDICATIONS AND USAGE

Just spray enough product in your palm to cover hands and rub hands together briskly until dry.

Children under 6 years of age should be supervised when using Sense Fresh.

Hand sanitizer to help reduce bacteria on the skin that could cause disease. Recommended for repeated use.

WARNINGS

■ Flammable. Keep away from fire or flame.

■ For external use only.

■ Do not use in eyes.

■ lf swallowed, get medical help promptly.

■ Stop use, ask doctor lf irritation occurs.

■ Keep out of reach of children.

DOSAGE AND ADMINISTRATION

for external use only

INACTIVE INGREDIENT

Water, Isopropyl Alcohol, Aloe Barbadensis Leaf Juice, propolis extract, Caprylyl Glycol, Glycerin, Isopropyl Myristate, Tocopheryl Acetate, Acrylates C10 30 Alkyl Acrylate Crosspolymer, Aminomethyl Propanol, Fragrance